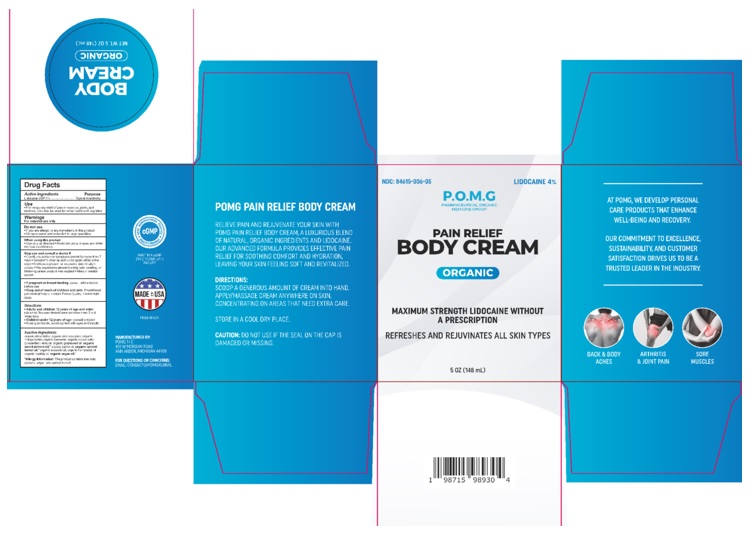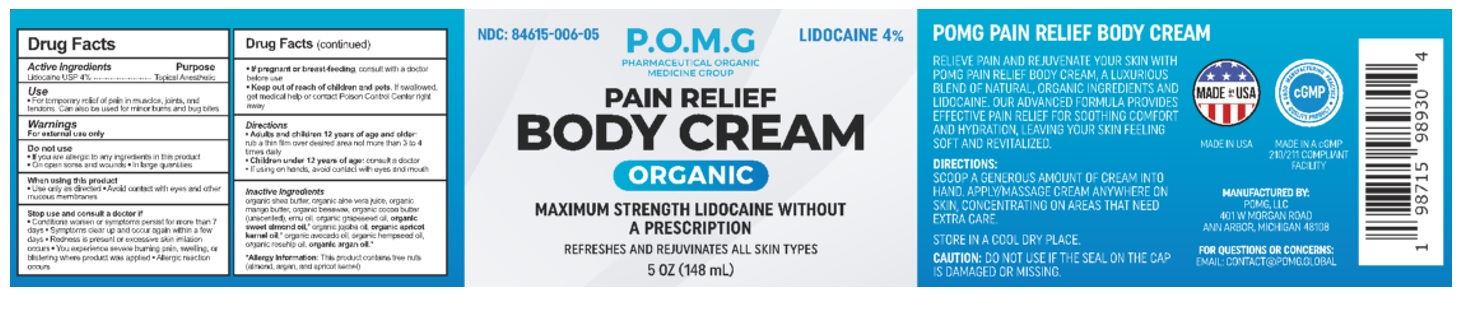 DRUG LABEL: POMG PAIN RELIEF BODY
NDC: 84615-006 | Form: CREAM
Manufacturer: POMG LLC
Category: otc | Type: HUMAN OTC DRUG LABEL
Date: 20241206

ACTIVE INGREDIENTS: LIDOCAINE 40 mg/1 mL
INACTIVE INGREDIENTS: ALMOND OIL; EMU OIL; SHEA BUTTER; BEESWAX; GRAPE SEED OIL; APRICOT KERNEL OIL; MANGIFERA INDICA SEED BUTTER; ARGAN OIL; COCOA BUTTER; CANNABIS SATIVA SEED OIL; ALOE VERA LEAF; AVOCADO OIL; ROSA CANINA FRUIT OIL; JOJOBA OIL

POMG PAIN RELIEF BODY CREAM

Active Ingredients

Lidocaine USP 4%

Purpose

Lidocaine USP 4%................Topical Anesthetic

Use

- For temporary relief of pain in muscles, joints, and tendons
- Can also be used for minor burns and bug bites

Warnings

For external use only

Do not use

• If you are allergic to any ingredients in this product

• On open sores and wounds

• In large quantities

When using this product

• Use only as directed

• Avoid contact with eyes and other mucous membranes

Stop use and consult a doctor if

• Conditions worsen or symptoms persist for more than 7 days

• Symptoms clear up and occur again within a few days

• Redness is present or excessive skin irritation occurs

• You experience severe burning pain, swelling, or blistering where product was applied

• Allergic reaction occurs

PREGNANCY OR BREAST FEEDING

• If pregnant or breast-feeding, consult with a doctor before use

• Keep out of reach of children and pets. If swallowed, get medical help or contact Poison Control Center right away

Directions

• Adults and children 12 years of age and older: rub a thin film over desired area not more than 3 to 4 times daily

• Children under 12 years of age: consult a doctor

• If using on hands, avoid contact with eyes and mouth

Inactive Ingredients

organic shea butter, organic aloe vera juice, organic mango butter, organic beeswax, organic cocoa butter (unscented), emu oil, organic grapeseed oil, organic sweet almond oil,* organic jojoba oil, organic apricot kernel oil,* organic avocado oil, organic hempseed oil, organic rosehip oil, organic argan oil.*

*Allergy Information: This product contains tree nuts (almond, argan, and apricot kernel)

PACKAGE LABEL

NDC: 84615-006-05

Lidocaine 4%

P.O.M.G.

Pharmaceutical Organic Medicine Group

Pain Relief

Body Cream

Organic

Maximum Strength Lidocaine Without a Prescription

Refreshes and Rejuvinates All Skin Types

5 oz (148 mL)